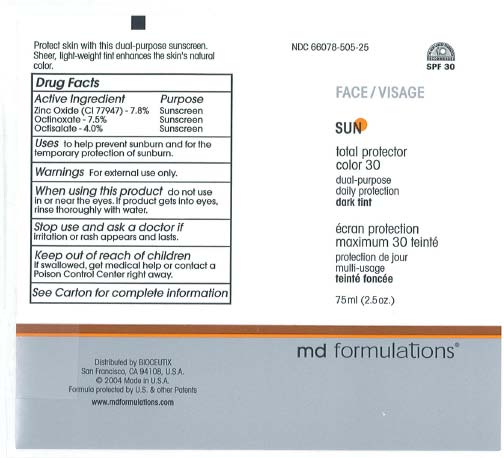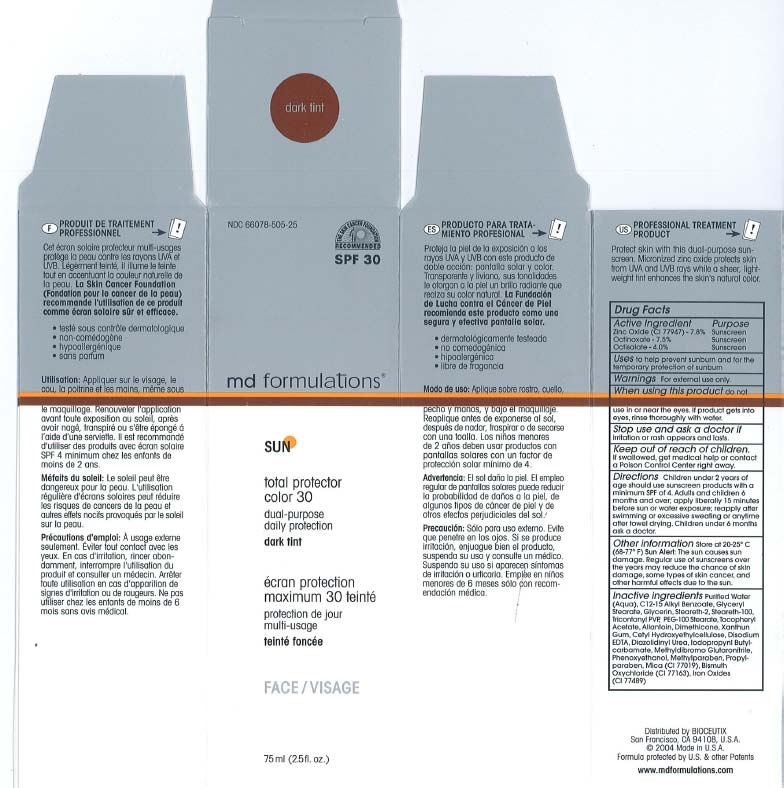 DRUG LABEL: Sun Total Protector Color 30 Dark Tint
NDC: 66078-505 | Form: CREAM
Manufacturer: MD Formulations
Category: otc | Type: HUMAN OTC DRUG LABEL
Date: 20100816

ACTIVE INGREDIENTS: Zinc Oxide 7.8 mL/100 mL; Octisalate 4 mL/100 mL; Octinoxate 7.5 mL/100 mL

Total Protector Color 30 dark tint

ACTIVE INGREDIENT

Zinc Oxide - 7.8%
Octlnoxote - 7.5%
Octlsolote - 4.0%

PURPOSE

Zinc Oxide - 7.8% Sunscreen
Octlnoxote - 7.5% Sunscreen
Octlsolote - 4.0% Sunscreen

When using this product do not use In or near the eyes. If product gets Into eyes, rinse thoroughly with water.

INDICATIONS AND USAGE

Uses to help prevent sunburn and for the temporary protection of sunburn.

Warnings : For external use only.

Stop use and ask a doctor if irritation or rash appears and lasts.

Keep out of reach of children. If swallowed, get medical help or contact a Polson Control Center right away.

DOSAGE AND ADMINISTRATION

Children under 2 years of age should use sunscreen products with a minimum SPF of 4. Adults and children 6 months and over; apply liberally 15 minutes before sun or water exposure; reapply after swimming or excessive sweating or anytime after towel drying. Children under 6 months
ask a doctor.

Other information Store at 20-25C (68 - 77F) Sun Alert: The sun causes sun damage. Regular use of sunscreens over the years may reduce the chance of skin damage, some types of skin cancer, and other harmful effects due to the sun.

INACTIVE INGREDIENT

Inactive ingredients: Purified Water (Aqua), C12-15 Alkyl Benzoate, Glyceryl Stearate, Glycerin, Stearelh·2, Stearelh-100, Trlcontanyl PVP, PEG-100 stearate, Tocopheryl Acetate, Allontoln, Dlmethlcone, Xanthun Gum, Cetyl Hydroxyethylcellulose, Disodium EDTA, Dlazolldlnyl Urea, lodopropynl Butylcarbamate, Methyldlbromo Glutaronllrlle, Phenoxyethcnol, Methylparaben, Propylparaben, MIca (CI 77019), Blsmulh OxychlorIde (CI 77163), Iron Oxides (CI77489)